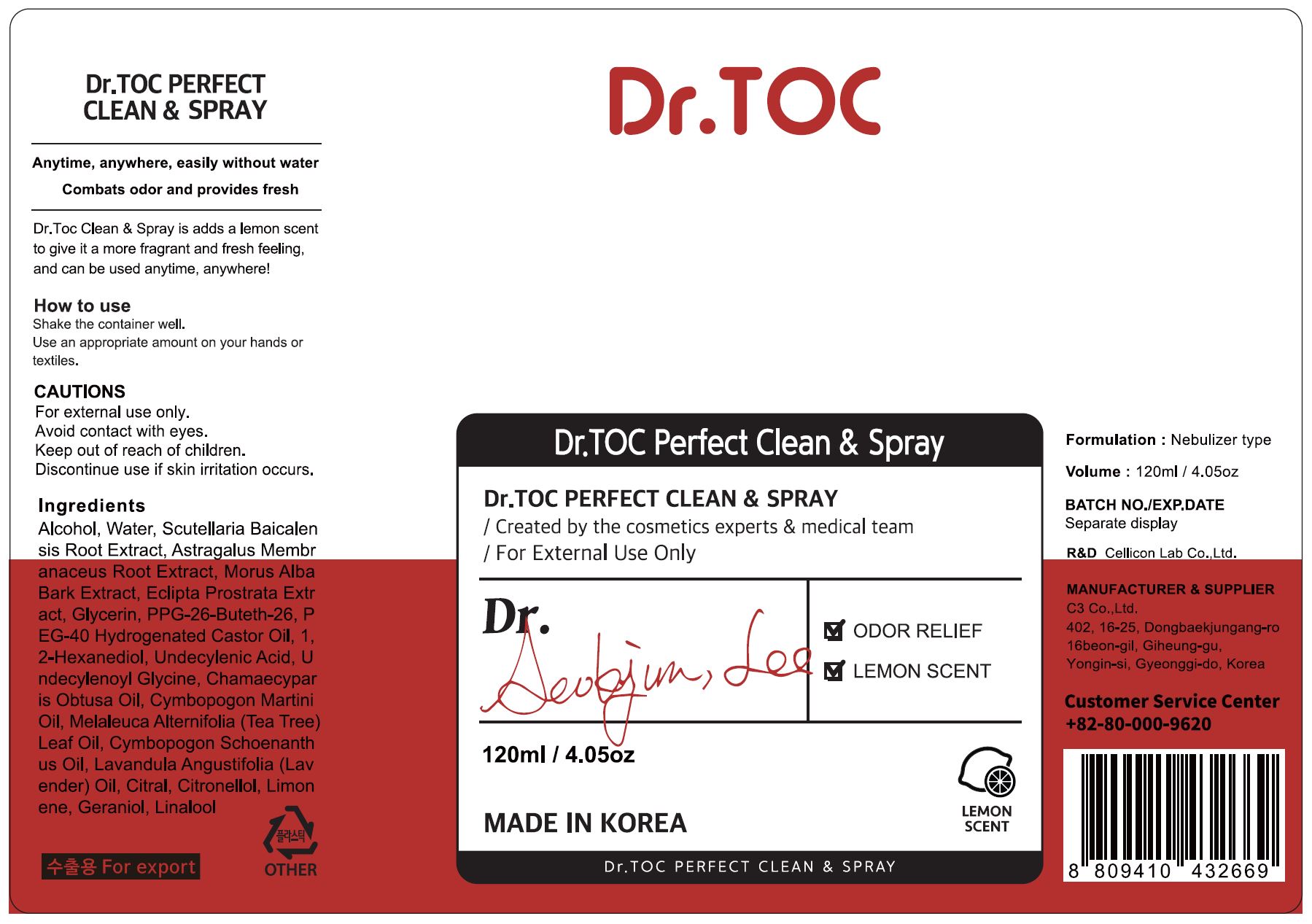 DRUG LABEL: Dr Toc Perfect CleanSpray
NDC: 70818-027 | Form: SPRAY
Manufacturer: C3 Co., Ltd.
Category: otc | Type: HUMAN OTC DRUG LABEL
Date: 20210214

ACTIVE INGREDIENTS: ALCOHOL 70.01 mL/100 mL
INACTIVE INGREDIENTS: WATER

C3 Co., Ltd. - isLeaf Hand Cleaning Gel

ACTIVE INGREDIENT

Alcohol

INACTIVE INGREDIENT

Water, Scutellaria Baicalen
sis Root Extract, Astragalus Membr
anaceus Root Extract, Morus Alba
Bark Extract, Eclipta Prostrata Extr
act, Glycerin, PPG-26-Buteth-26, P
EG-40 Hydrogenated Castor Oil, 1,
2-Hexanediol, Undecylenic Acid, U
ndecylenoyl Glycine, Chamaecypar
is Obtusa Oil, Cymbopogon Martini
Oil, Melaleuca Alternifolia (Tea Tree)
Leaf Oil, Cymbopogon Schoenanth
us Oil, Lavandula Angustifolia (Lav
ender) Oil, Citral, Citronellol, Limon
ene, Geraniol, Linalool

PURPOSE

Antiseptic

keep out of reach of the children

INDICATIONS AND USAGE

Shake the container well.
Use an appropriate amount on your hands or textiles.

WARNINGS

For external use only.

Avoid contact with eyes.

Keep out of reach of children.

Discontinue use if skin irritation occurs.

DOSAGE AND ADMINISTRATION

for external use only